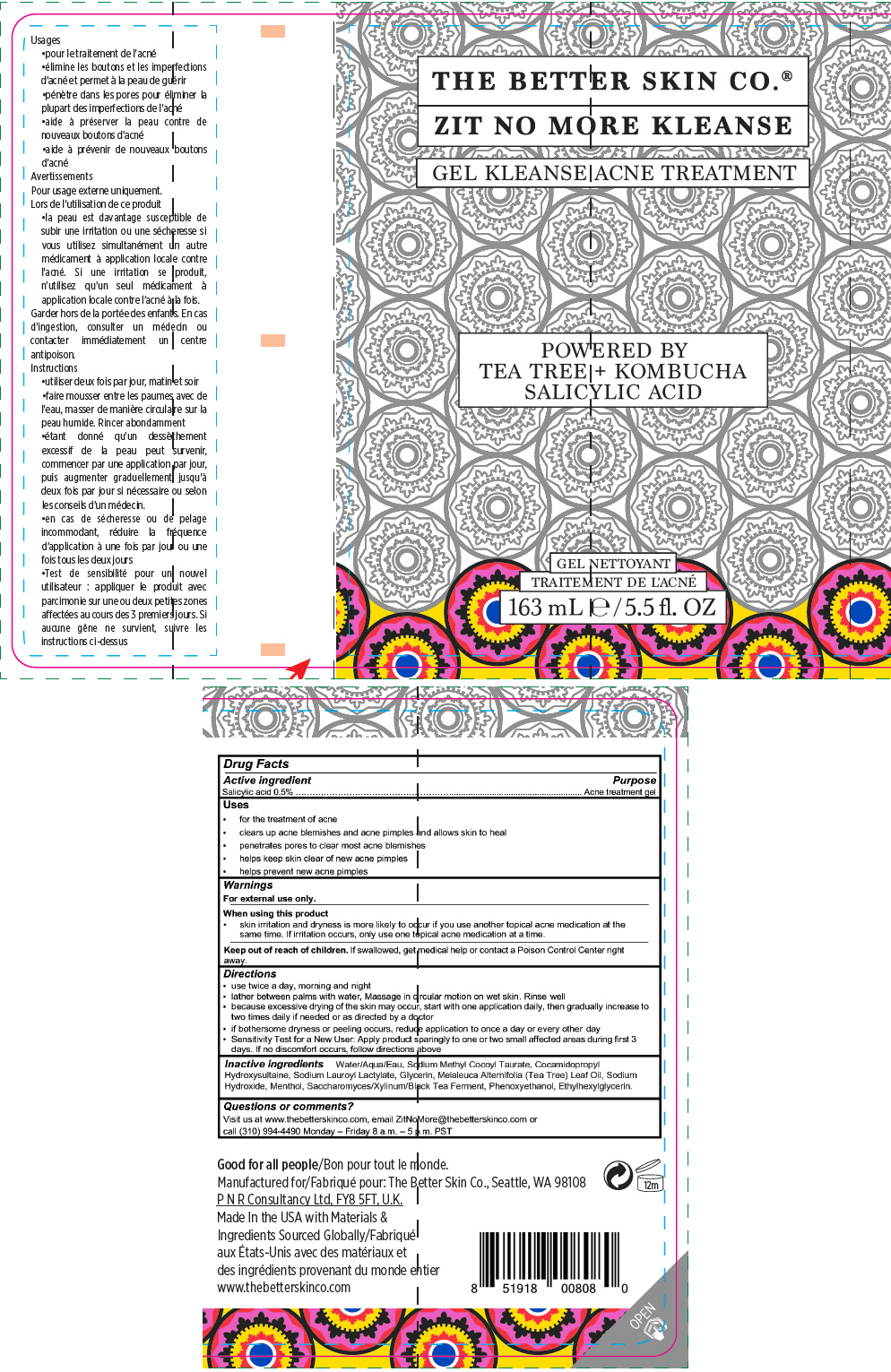 DRUG LABEL: THE BETTER SKIN CO. 
NDC: 71716-101 | Form: GEL
Manufacturer: Mirakle Cosmetics LLC dbaThe Better Skin Co.
Category: otc | Type: HUMAN OTC DRUG LABEL
Date: 20200626

ACTIVE INGREDIENTS: salicylic acid 5 mg/1 mL
INACTIVE INGREDIENTS: WATER; SODIUM METHYL COCOYL TAURATE; COCAMIDOPROPYL HYDROXYSULTAINE; SODIUM LAUROYL LACTYLATE; GLYCERIN; TEA TREE OIL; SODIUM HYDROXIDE; MENTHOL, UNSPECIFIED FORM; PHENOXYETHANOL; ETHYLHEXYLGLYCERIN

THE BETTER SKIN CO.®
ZIT NO MORE KLEANSE

Drug Facts

Active ingredient

Salicylic acid 0.5%

Purpose

Acne treatment gel

Uses

- for the treatment of acne
- clears up acne blemishes and acne pimples and allows skin to heal
- penetrates pores to clear most acne blemishes
- helps keep skin clear of new acne pimples
- helps prevent new acne pimples

Warnings

For external use only.

When using this product

- skin irritation and dryness is more likely to occur if you use another topical acne medication at the same time. If irritation occurs, only use one topical acne medication at a time.

Keep out of reach of children. If swallowed, get medical help or contact a Poison Control Center right away.

Directions

- use twice a day, morning and night
- lather between palms with water, Massage in circular motion on wet skin. Rinse well
- because excessive drying of the skin may occur, start with one application daily, then gradually increase to two times daily if needed or as directed by a doctor
- if bothersome dryness or peeling occurs, reduce application to once a day or every other day
- Sensitivity Test for a New User: Apply product sparingly to one or two small affected areas during first 3 days. If no discomfort occurs, follow directions above

Inactive ingredients

Water/Aqua/Eau, Sodium Methyl Cocoyl Taurate, Cocamidopropyl Hydroxysultaine, Sodium Lauroyl Lactylate, Glycerin, Melaleuca Alternifolia (Tea Tree) Leaf Oil, Sodium Hydroxide, Menthol, Saccharomyces/Xylinum/Black Tea Ferment, Phenoxyethanol, Ethylhexylglycerin.

Questions or comments?

Visit us at www.thebetterskinco.com, email ZitNoMore@thebetterskinco.com or call (310) 994-4490 Monday – Friday 8 a.m. – 5 p.m. PST

PRINCIPAL DISPLAY PANEL - 163 mL Bottle Label

THE BETTER SKIN CO.®
ZIT NO MORE KLEANSE

GEL KLEANSE ACNE TREATMENT

POWERED BY
TEA TREE + KOMBUCHA
SALICYLIC ACID

163 mL ℮ /5.5 fl. OZ